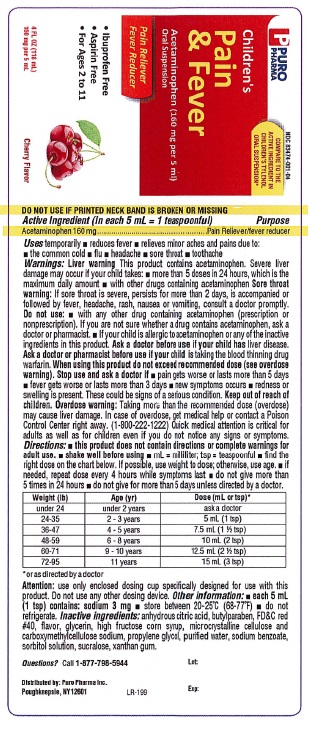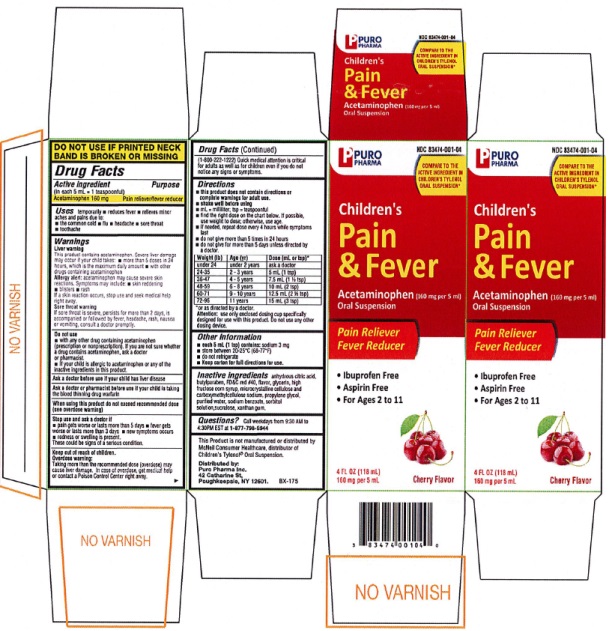 DRUG LABEL: Childrens Pain Relief and Fever Reducer Oral Suspension Cherry
NDC: 83474-001 | Form: SUSPENSION
Manufacturer: Puro Pharma Inc.
Category: otc | Type: HUMAN OTC DRUG LABEL
Date: 20251227

ACTIVE INGREDIENTS: ACETAMINOPHEN 160 mg/5 mL
INACTIVE INGREDIENTS: ANHYDROUS CITRIC ACID; BUTYLPARABEN; FD&C RED NO. 40; GLYCERIN; HIGH FRUCTOSE CORN SYRUP; CELLULOSE, MICROCRYSTALLINE; CARBOXYMETHYLCELLULOSE SODIUM; PROPYLENE GLYCOL; WATER; SODIUM BENZOATE; SORBITOL SOLUTION; SUCRALOSE; XANTHAN GUM

Children's Pain Relief & Fever Reducer Oral Suspension Cherry

Drug Facts

Active ingredient
(in each 5 mL = 1 teaspoonful)
Acetaminophen 160 mg

Purpose
Pain reliever/fever reducer

INDICATIONS AND USAGE

Usestemporarily ■ reduces fever
■ relieves minor aches and pains due to:
■ the common cold ■ flu ■ headache ■ sore throat
■ toothache

Warnings
Liver warning
This product contains acetaminophen. Severe liver
damage may occur if your child takes: ■ more than 5
doses in 24 hours, which is the maximum daily amount
■ with other drugs containing acetaminophen

Allergy alert:acetaminophen may cause severe skin
reactions. Symptoms may include: ■ skin reddening
■ blisters ■ rash
If a skin reaction occurs, stop use and seek medical help
right away.

Sore throat warning
If sore throat is severe, persists for more than 2 days,
is accompanied or followed by fever, headache, rash,
nausea or vomiting, consult a doctor promptly.

Do not use
■ with any other drug containing acetaminophen
(prescription or nonprescription). If you are not sure
whether a drug contains acetaminophen, ask a doctor
or pharmacist.
■ If your child is allergic to acetaminophen or any other of
the inactive ingredients in this product.

Ask a doctor before use if your childhas liver disease.

Ask a doctor or pharmacist before use if your child

istaking the blood thinning drug warfarin.

When using this product do not exceed

recommended dose (see overdose warning)

Stop use and ask a doctor if
■ pain gets worse or lasts more than 5 days ■ fever
gets worse or lasts more than 3 days ■ new
symptoms occur ■ redness or swelling is present.
These could be signs of a serious condition.

Keep out of reach of children.

OVERDOSAGE

Overdose warning:Taking more than the recommended dose (overdose)
may cause liver damage. In case of overdose, get
medical help or contact a Poison Control Center right
away. (1-800-222-1222) Quick medical attention is critical
for adults as well as for children even if you
do not notice any signs or symptoms.

Directions
■ this product does not contain directions or
complete warnings for adult use.
■ shake well before using
■ mL = milliliter; tsp = teaspoonful
■ find the right dose on the chart below. If possible, use
weight to dose, otherwise, use age.
■ if needed, repeat dose every 4 hours while
symptoms last
■ do not give more than 5 times in 24 hours
■ do not give for more than 5 days unless directed
by a doctor.

Weight (lb) | Age (yr) | Dose (mL or tsp)*
under 24 | under 2 years | ask a doctor
24-35 | 2 - 3 years | 5 mL (1 tsp)
36-47 | 4 - 5 years | 7.5 mL (1 1/2 tsp)
48-59 | 6 - 8 years | 10 mL (2 tsp)
60-71 | 9 - 10 years | 12.5. mL (2 1/2 tsp)
72-95 | 11 years | 15 mL (3 tsp)

*or as directed by a doctor

Attention:use only enclosed dosing cup specifically
designed for use with this product. Do not use any
other dosing device.

Other information
■ each 5 mL (1 tsp) contains; sodium 3 mg
■ store between 20-25ºC (68-77ºF)
■ do not refrigerate
■ Keep carton for full directions for use.

Inactive ingredients anhydrous citric acid,
butylparaben, FD&C red #40, flavor, glycerin, high
fructose corn syrup, microcrystalline cellulose and
carboxymethylcellulose sodium, propylene glycol,
purified water, sodium benzoate, sorbitol solution,
sucralose, xanthan gum.

Questions?Call 1-877-798-5944

Package Labeling PURO PHARMA Children's Pain & Fever Acetaminophen Oral Suspension Cherry Flavor

PURO

PHARMA NDC 83474-001-04

COMPARE TO THE

ACTIVE INGREDIENT

IN CHILDREN'S TYLENOL

ORAL SUSPENSION*

PURO

PHARMA

Children's Pain & Fever

Acetaminophen

Oral Suspension

Pain reliever

Fever Reducer

• Ibuprofen Free
• Aspirin Free
• For Ages 2 to 11

4 FL OZ (118 mL)

160 mg per 5 mL

Cherry Flavor

This product is not manufactured or distributed by McNeil

Consumer Healthcare, distributor of Children's Tylenol®

Oral Suspensin

Distributed by:

Puro Pharma Inc.

42 Catharine St. Poughkeepsie, NY 12601

Info@puro-pharma.com

BX-175

res